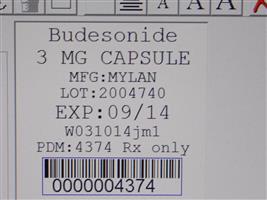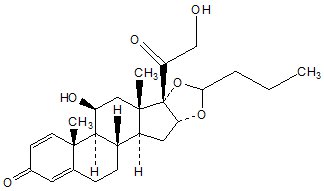 DRUG LABEL: Budesonide
NDC: 68151-4374 | Form: CAPSULE
Manufacturer: Carilion Materials Management
Category: prescription | Type: HUMAN PRESCRIPTION DRUG LABEL
Date: 20140305

ACTIVE INGREDIENTS: BUDESONIDE 3 mg/1 1
INACTIVE INGREDIENTS: ACETYLTRIBUTYL CITRATE; SILICON DIOXIDE; CROSPOVIDONE; DIMETHICONE; ETHYLCELLULOSES; FD&C RED NO. 40; GELATIN; LACTOSE MONOHYDRATE; MAGNESIUM STEARATE; METHACRYLIC ACID - ETHYL ACRYLATE COPOLYMER (1:1) TYPE A; POLYSORBATE 80; SODIUM HYDROXIDE; SODIUM LAURYL SULFATE; TALC; TITANIUM DIOXIDE; TRIETHYL CITRATE; FERROSOFERRIC OXIDE; D&C YELLOW NO. 10; FD&C BLUE NO. 1; FD&C BLUE NO. 2; PROPYLENE GLYCOL; SHELLAC

HIGHLIGHTS OF PRESCRIBING INFORMATION

These highlights do not include all the information needed to use safely and effectively. See full prescribing information for . Initial U.S. Approval: 1997 budesonide capsules (enteric coated) budesonide capsules (enteric coated)
BUDESONIDE capsules (enteric coated), for oral use

1 INDICATIONS AND USAGE

Budesonide capsules (enteric coated) are a glucocorticosteroid indicated for:

- Treatment of mild to moderate active Crohn’s disease involving the ileum and/or the ascending colon. () 1.1
- Maintenance of clinical remission of mild to moderate Crohn’s disease involving the ileum and/or the ascending colon for up to 3 months. () 1.2

2 DOSAGE AND ADMINISTRATION

- Mild to moderate active Crohn’s disease: 9 mg once daily in the morning for up to 8 weeks. Repeated 8 week courses of budesonide capsules (enteric coated) can be given for recurring episodes of active disease. () 2.1
- Maintenance of clinical remission of mild to moderate Crohn’s disease: 6 mg once daily for up to 3 months. Continued treatment with budesonide capsules (enteric coated) 6 mg for more than 3 months has not been shown to provide substantial clinical benefit. () 2.2

3 DOSAGE FORMS AND STRENGTHS

Capsules: 3 mg () 3

4 CONTRAINDICATIONS

Hypersensitivity to any of the ingredients in budesonide capsules (enteric coated). () 4

5 WARNINGS AND PRECAUTIONS

- Since budesonide capsules (enteric coated) are a glucocorticosteroid, general warnings concerning glucocorticoids should be followed. () Hypercorticism and adrenal suppression:5.1
- Care is needed in patients who are transferred from glucocorticosteroid treatment with high systemic effects to corticosteroids with lower systemic availability, such as budesonide capsules (enteric coated). () Transferring patients from systemic glucocorticosteroid therapy:5.2
- Potential worsening of infections (e.g., existing tuberculosis, fungal, bacterial, viral, or parasitic infection). Use with caution in patients with these infections. More serious or even fatal course of chickenpox or measles can occur in susceptible patients. () Immunosuppression:5.3

6 ADVERSE REACTIONS

Most common adverse reactions (≥ 5%) are headache, respiratory infection, nausea, back pain, dyspepsia, dizziness, abdominal pain, flatulence, vomiting, fatigue, pain. () 6.1

To report SUSPECTED ADVERSE REACTIONS, contact Mylan Pharmaceuticals Inc. at 1-877-446-3679 (1-877-4-INFO-RX) or FDA at 1-800-FDA-1088 orwww.fda.gov/medwatch.

7 DRUG INTERACTIONS

- Cytochrome P450 3A4 inhibitors (e.g., ketoconazole, grapefruit juice) should be avoided. May cause increased systemic corticosteroid effects. (, ,) 2.3712.3

8 USE IN SPECIFIC POPULATIONS

- Hepatic Insufficiency: Monitor patients for signs and/or symptoms of hypercorticism. (,) 5.48.6

FULL PRESCRIBING INFORMATION

1 INDICATIONS AND USAGE

1.1 Mild to Moderate Active Crohn’s Disease

Budesonide capsules (enteric coated) are indicated for the treatment of mild to moderate active Crohn's disease involving the ileum and/or the ascending colon.

1.2 Maintenance of Clinical Remission of Mild to Moderate Crohn’s Disease

Budesonide capsules (enteric coated) are indicated for the maintenance of clinical remission of mild to moderate Crohn’s disease involving the ileum and/or the ascending colon for up to 3 months.

2 DOSAGE AND ADMINISTRATION

2.1 Mild to Moderate Active Crohn’s Disease

The recommended adult dosage for the treatment of mild to moderate active Crohn's disease involving the ileum and/or the ascending colon is 9 mg orally taken once daily in the morning for up to 8 weeks. Repeated 8 week courses of budesonide capsules (enteric coated) can be given for recurring episodes of active disease.

2.2 Maintenance of Clinical Remission of Mild to Moderate Crohn’s Disease

Following an 8 week course(s) of treatment for active disease and once the patient’s symptoms are controlled (CDAI less than 150), budesonide capsules (enteric coated) 6 mg orally is recommended once daily for maintenance of clinical remission up to 3 months. If symptom control is still maintained at 3 months an attempt to taper to complete cessation is recommended. Continued treatment with budesonide capsules (enteric coated) 6 mg for more than 3 months has not been shown to provide substantial clinical benefit.

Patients with mild to moderate active Crohn’s disease involving the ileum and/or ascending colon have been switched from oral prednisolone to budesonide capsules (enteric coated) with no reported episodes of adrenal insufficiency. Since prednisolone should not be stopped abruptly, tapering should begin concomitantly with initiating budesonide capsule (enteric coated) treatment.

2.3 CYP3A4 inhibitors

If concomitant administration with ketoconazole, or any other CYP3A4 inhibitor, is indicated, patients should be closely monitored for increased signs and/or symptoms of hypercorticism. Grapefruit juice, which is known to inhibit CYP3A4, should also be avoided when taking budesonide capsules (enteric coated). In these cases, reduction in the dose of budesonide capsules (enteric coated) should be considered [ ]. see and Drug Interactions (7) Clinical Pharmacology (12.3)

3 DOSAGE FORMS AND STRENGTHS

Budesonide capsules (enteric coated) 3 mg have a red opaque cap and red opaque body, hard shell gelatin capsule filled with white to off-white enteric-coated pellets with no markings. The capsules are axially printed with over in black ink on both the cap and body. MYLAN 7155

4 CONTRAINDICATIONS

Budesonide capsules (enteric coated) are contraindicated in patients with hypersensitivity to budesonide or any of the ingredients of budesonide capsules (enteric coated). Anaphylactic reactions have occurred [ ]. see Adverse Reactions (6.2)

5 WARNINGS AND PRECAUTIONS

5.1 Hypercorticism and Adrenal Suppression

When glucocorticosteroids are used chronically, systemic effects such as hypercorticism and adrenal suppression may occur. Glucocorticosteroids can reduce the response of the hypothalamus-pituitary-adrenal (HPA) axis to stress. In situations where patients are subject to surgery or other stress situations, supplementation with a systemic glucocorticosteroid is recommended. Since budesonide capsules (enteric coated) are a glucocorticosteroid, general warnings concerning glucocorticoids should be followed.

5.2 Transferring Patients from Systemic Glucocorticosteroid Therapy

Care is needed in patients who are transferred from glucocorticosteroid treatment with high systemic effects to corticosteroids with lower systemic availability, such as budesonide capsules (enteric coated), since symptoms attributed to withdrawal of steroid therapy, including those of acute adrenal suppression or benign intracranial hypertension, may develop. Adrenocortical function monitoring may be required in these patients and the dose of glucocorticosteroid treatment with high systemic effects should be reduced cautiously.

5.3 Immunosuppression

Patients who are on drugs that suppress the immune system are more susceptible to infection than healthy individuals. Chicken pox and measles, for example, can have a more serious or even fatal course in susceptible patients or patients on immunosuppressant doses of glucocorticosteroids. In patients who have not had these diseases, particular care should be taken to avoid exposure.

How the dose, route and duration of glucocorticosteroid administration affect the risk of developing a disseminated infection is not known. The contribution of the underlying disease and/or prior glucocorticosteroid treatment to the risk is also not known. If exposed, therapy with varicella zoster immune globulin (VZIG) or pooled intravenous immunoglobulin (IVIG), as appropriate, may be indicated. If exposed to measles, prophylaxis with pooled intramuscular immunoglobulin (IG) may be indicated. (See prescribing information for VZIG and IG.) If chicken pox develops, treatment with antiviral agents may be considered.

Glucocorticosteroids should be used with caution, if at all, in patients with active or quiescent tuberculosis infection, untreated fungal, bacterial, systemic viral or parasitic infections.

Replacement of systemic glucocorticosteroids with budesonide capsules (enteric coated) may unmask allergies (e.g., rhinitis and eczema), which were previously controlled by the systemic drug.

5.4 Increased Systemic Glucocorticosteroid Susceptibility

Reduced liver function affects the elimination of glucocorticosteroids, and increased systemic availability of oral budesonide has been demonstrated in patients with liver cirrhosis [ ]. see Use in Specific Populations (8.6)

5.5 Other Glucocorticosteroid Effects

Caution should be taken in patients with hypertension, diabetes mellitus, osteoporosis, peptic ulcer, glaucoma or cataracts, or with a family history of diabetes or glaucoma, or with any other condition where glucocorticosteroids may have unwanted effects.

6 ADVERSE REACTIONS

Systemic glucocorticosteroid use may result in the following:

- Hypercorticism and Adrenal Suppression [ ] see Warnings and Precautions (5.1)
- Symptoms of steroid withdrawal in those patients transferring from Systemic Glucocorticosteroid Therapy [ ] see Warnings and Precautions (5.2)
- Immunosuppression [ ] see Warnings and Precautions (5.3)
- Increased Systemic Glucocorticosteroid Susceptibilty [ ] see Warnings and Precautions (5.4)
- Other Glucocorticosteroid Effects [ ] see Warnings and Precautions (5.5)

6.1 Clinical Trials Experience

Because clinical trials are conducted under widely varying conditions, adverse reaction rates observed in the clinical trials of a drug cannot be directly compared to rates in the clinical trials of another drug and may not reflect the rates observed in practice.

The safety of budesonide capsules (enteric coated) was evaluated in 651 patients in five short-term, active disease state studies. They ranged in age from 17 to 74 (mean 35), 40% were male and 97% were white, 2.6% were greater than or equal to 65 years of age. Five hundred and twenty patients were treated with budesonide capsules (enteric coated) 9 mg (total daily dose). The most common adverse reactions reported were headache, respiratory infection, nausea, and symptoms of hypercorticism. Clinical studies have shown that the frequency of glucocorticosteroid-associated adverse reactions was substantially reduced with budesonide capsules (enteric coated) compared with prednisolone at therapeutically equivalent doses. Adverse reactions occurring in greater than or equal to 5% of the patients are listed in Table 1:

Table 1. Adverse Reactions Occurring in Greater Than or Equal to 5% of the Patients in Any Treated Group
 | Budesonide Capsules (Enteric Coated); 9 mg; n = 520 | Placebo; n = 107 | Prednisolone; 40 mg; n = 145 | Comparator [This drug is not approved for the treatment of Crohn’s disease in the United States.]; n = 88
Adverse Reaction | Number (%) | Number (%) | Number (%) | Number (%)
Headache | 107(21) | 19(18) | 31(21) | 11(13)
Respiratory Infection | 55(11) | 7(7) | 20(14) | 5(6)
Nausea | 57(11) | 10(9) | 18(12) | 7(8)
Back Pain | 36(7) | 10(9) | 17(12) | 5(6)
Dyspepsia | 31(6) | 4(4) | 17(12) | 3(3)
Dizziness | 38(7) | 5(5) | 18(12) | 5(6)
Abdominal Pain | 32(6) | 18(17) | 6(4) | 10(11)
Flatulence | 30(6) | 6(6) | 12(8) | 5(6)
Vomiting | 29(6) | 6(6) | 6(4) | 6(7)
Fatigue | 25(5) | 8(7) | 11(8) | 0(0)
Pain | 24(5) | 8(7) | 17(12) | 2(2)

The safety of budesonide capsules (enteric coated) was evaluated in 233 patients in four long-term clinical trials (52 weeks). A total of 145 patients were treated with budesonide capsules (enteric coated) 6 mg. A total of 8% of budesonide capsule (enteric coated) patients discontinued treatment due to adverse reactions compared with 10% in the placebo group. The adverse reaction profile in long-term treatment of Crohn’s disease was similar to that of short-term treatment with budesonide capsules (enteric coated) 9 mg in active Crohn’s disease.

In the long-term clinical trials, the following adverse reactions occurred in greater than or equal to 5% of the 6 mg budesonide capsule (enteric coated) patients and are not listed in (Table 1) or by body system below: diarrhea (10%); sinusitis (8%); infection viral (6%); and arthralgia (5%).

Adverse reactions, occurring in patients treated with budesonide capsules (enteric coated) 9 mg (total daily dose) in short-term active disease state studies and/or budesonide capsules (enteric coated) 6 mg (total daily dose) long-term, with an incidence less than 5% and greater than placebo are listed below by system organ class:

leukocytosis Blood and lymphatic system disorders:
palpitation, tachycardia Cardiac disorders:
eye abnormality, vision abnormal Eye disorders:
asthenia, chest pain, dependent edema, face edema, flu-like disorder, malaise, fever General disorders and administration site conditions:
anus disorder, Crohn’s disease aggravated, enteritis, epigastric pain, gastrointestinal fistula, glossitis, hemorrhoids, intestinal obstruction, tongue edema, tooth disorder Gastrointestinal disorders:
Ear infection-not otherwise specified, bronchitis, abscess, rhinitis, urinary tract infection, thrush Infections and infestations:
c-reactive protein increased, weight increased Investigations:
appetite increased, hypokalemia Metabolism and nutrition disorders:
arthritis, cramps, myalgia Musculoskeletal and connective tissue disorders:
hyperkinesia, parasthesia, tremor, vertigo, dizziness, somnolence, amnesia Nervous system disorders:
agitation, confusion, insomnia, nervousness, sleep disorder Psychiatric disorders:
dysuria, micturition frequency, nocturia Renal and urinary disorders:
intermenstrual bleeding, menstrual disorder Reproductive system and breast disorders:
dyspnea, pharynx disorder Respiratory, thoracic and mediastinal disorders:
acne, alopecia, dermatitis, eczema, skin disorder, sweating increased, purpura Skin and subcutaneous tissue disorders:
flushing, hypertension Vascular disorders:

Table 2 displays the frequency and incidence of signs/symptoms of hypercorticism by active questioning of patients in short-term clinical trials.

Table 2. Summary and Incidence of Signs/Symptoms of Hypercorticism in Short-Term Studies
 | Budesonide Capsules (Enteric Coated); 9 mg; n = 427 | Placebo; n = 107 | Prednisolone; Taper 40 mg; n = 145
Signs/Symptom | Number (%) | Number (%) | Number (%)
Acne | 63(15) | 14(13) | 33(23) [Statistically significantly different from budesonide capsules (enteric coated) 9 mg.]
Bruising Easily | 63(15) | 12(11) | 13(9)
Moon Face | 46(11) | 4(4) | 53(37)
Swollen Ankles | 32(7) | 6(6) | 13(9)
Hirsutism [Adverse reaction dictionary included term hair growth increased, local and hair growth increased, general.] | 22(5) | 2(2) | 5(3)
Buffalo Hump | 6(1) | 2(2) | 5(3)
Skin Striae | 4(1) | 2(2) | 0(0)

Table 3 displays the frequency and incidence of signs/symptoms of hypercorticism by active questioning of patients in long-term clinical trials.

Table 3. Summary and Incidence of Symptoms of Hypercorticism in Long-Term Studies
 | Budesonide Capsules (Enteric Coated); 3 mg; n = 88 | Budesonide Capsules (Enteric Coated); 6 mg; n = 145 | Placebo; n = 143
Signs/Symptom | Number (%) | Number (%) | Number (%)
Bruising Easily | 4(5) | 15(10) | 5(4)
Acne | 4(5) | 14(10) | 3(2)
Moon Face | 3 (3) | 6(4) | 0
Hirsutism | 2 (2) | 5(3) | 1(1)
Swollen Ankles | 2 (2) | 3(2) | 3(2)
Buffalo Hump | 1 (1) | 1 (1) | 0
Skin Striae | 2 (2) | 0 | 0

The incidence of signs/symptoms of hypercorticism as described above in long-term clinical trials was similar to that seen in the short-term clinical trials.

A randomized, open, parallel-group multicenter safety study specifically compared the effect of budesonide capsules (enteric coated) (less than 9 mg per day) and prednisolone (less than 40 mg per day) on bone mineral density over 2 years when used at doses adjusted to disease severity. Bone mineral density decreased significantly less with budesonide capsules (enteric coated) than with prednisolone in steroid-naïve patients, whereas no difference could be detected between treatment groups for steroid-dependent patients and previous steroid users. The incidence of symptoms associated with hypercorticism was significantly higher with prednisolone treatment.

Clinical Laboratory Test Findings

The following potentially clinically significant laboratory changes in clinical trials, irrespective of relationship to budesonide capsules (enteric coated), were reported in greater than or equal to 1% of patients: hypokalemia, leukocytosis, anemia, hematuria, pyuria, erythrocyte sedimentation rate increased, alkaline phosphatase increased, atypical neutrophils, C-reactive protein increased, and adrenal insufficiency.

6.2 Postmarketing Experience

The following adverse reactions have been reported during post-approval use of budesonide capsules (enteric coated). Because these reactions are reported voluntarily from a population of uncertain size, it is not always possible to reliably estimate their frequency or establish a causal relationship to drug exposure.

Anaphylactic reactions Immune System Disorders:
Benign intracranial hypertension Nervous System Disorders:
Mood swings Psychiatric Disorders:

7 DRUG INTERACTIONS

Concomitant oral administration of ketoconazole (a known inhibitor of CYP3A4 activity in the liver and in the intestinal mucosa) caused an 8-fold increase of the systemic exposure to oral budesonide. If treatment with inhibitors of CYP3A4 activity (such as ketoconazole, itraconazole, ritonavir, indinavir, saquinavir, erythromycin, etc.) is indicated, reduction of the budesonide dose should be considered. After extensive intake of grapefruit juice (which inhibits CYP3A4 activity predominantly in the intestinal mucosa), the systemic exposure for oral budesonide increased about two times. Ingestion of grapefruit or grapefruit juice should be avoided in connection with budesonide administration [ ]. see Clinical Pharmacology (12.3)

8 USE IN SPECIFIC POPULATIONS

8.1 Pregnancy

Teratogenic Effects. Pregnancy Category C

Budesonide was teratogenic and embryocidal in rabbits and rats. Budesonide produced fetal loss, decreased pup weights, and skeletal abnormalities at subcutaneous doses of 25 mcg/kg in rabbits (approximately 0.05 times the maximum recommended human dose on a body surface area basis) and 500 mcg/kg in rats (approximately 0.5 times the maximum recommended human dose on a body surface area basis).

There are no adequate and well-controlled studies in pregnant women. Budesonide should be used during pregnancy only if the potential benefit justifies the potential risk to the fetus.

Nonteratogenic Effects

Hypoadrenalism may occur in infants born of mothers receiving corticosteroids during pregnancy. Such infants should be carefully observed.

8.3 Nursing Mothers

The disposition of budesonide when delivered by inhalation from a dry powder inhaler at doses of 200 or 400 mcg twice daily for at least 3 months was studied in eight lactating women with asthma from 1 to 6 months postpartum . Systemic exposure to budesonide in these women appears to be comparable to that in non-lactating women with asthma from other studies. Breast milk obtained over eight hours post-dose revealed that the maximum budesonide concentration for the 400 and 800 mcg total daily doses was 0.39 and 0.78 nmol/L, respectively, and occurred within 45 minutes after inhalation. The estimated oral daily dose of budesonide from breast milk to the infant is approximately 0.007 and 0.014 mcg/kg per day for the two dose regimens used in this study, which represents approximately 0.3% to 1% of the dose inhaled by the mother. Budesonide plasma concentrations obtained from five infants at about 90 minutes after breast feeding (and about 140 minutes after drug administration to the mother) were below quantifiable levels (less than 0.02 nmol/L in four infants and less than 0.04 nmol/L in one infant).^1

The recommended daily dose of budesonide capsules (enteric coated) is higher (up to 9 mg daily) compared with inhaled budesonide (up to 800 mg daily) given to mothers in the above study. The maximum budesonide plasma concentration following a 9 mg daily dose (in both single- and repeated-dose pharmacokinetic studies) of oral budesonide is approximately 5 to 10 nmol/L which is up to 10 times higher than the 1 to 2 nmol/L for a 800 mg daily dose of inhaled budesonide at steady state in the above inhalation study.

Since there are no data from controlled trials on the use of budesonide capsules (enteric coated) by nursing mothers or their infants, and because of the potential for serious adverse reactions in nursing infants from budesonide capsules (enteric coated), a decision should be made whether to discontinue nursing or to discontinue budesonide capsules (enteric coated), taking into account the clinical importance of budesonide capsules (enteric coated) to the mother.

Budesonide is secreted in human milk. Data from budesonide delivered via dry powder inhaler indicates that the total daily oral dose of budesonide available in breast milk to the infant is approximately 0.3% to 1% of the dose inhaled by the mother. Assuming the coefficient of extrapolation between the inhaled and oral doses is constant across all dose levels, at therapeutic doses of budesonide capsules (enteric coated), budesonide exposure to the nursing child may be up to 10 times higher than that by budesonide inhalation.

8.4 Pediatric Use

Safety and effectiveness in pediatric patients have not been established. Systemic and inhaled corticosteroids, including budesonide capsules (enteric coated), may cause a reduction of growth velocity in pediatric patients.

8.5 Geriatric Use

Clinical studies of budesonide capsules (enteric coated) did not include sufficient numbers of subjects aged 65 and over to determine whether they respond differently from younger subjects. Other reported clinical experience has not identified differences in responses between the elderly and younger patients. In general, dose selection for an elderly patient should be cautious, usually starting at the low end of the dosing range, reflecting the greater frequency of decreased hepatic, renal, or cardiac function, and of concomitant disease or other drug therapy.

8.6 Hepatic Insufficiency

Patients with moderate to severe liver disease should be monitored for increased signs and/or symptoms of hypercorticism. Reducing the dose of budesonide capsules (enteric coated) should be considered in these patients [ ]. see Warnings and Precautions (5.4)

10 OVERDOSAGE

Reports of acute toxicity and/or death following overdosage of glucocorticosteroids are rare. Treatment consists of immediate gastric lavage or emesis followed by supportive and symptomatic therapy.

If glucocorticosteroids are used at excessive doses for prolonged periods, systemic glucocorticosteroid effects such as hypercorticism and adrenal suppression may occur. For chronic overdosage in the face of severe disease requiring continuous steroid therapy, the dosage may be reduced temporarily.

Single oral doses of 200 and 400 mg/kg were lethal in female and male mice, respectively. The signs of acute toxicity were decreased motor activity, piloerection and generalized edema.

11 DESCRIPTION

Budesonide the active ingredient of budesonide capsules (enteric coated), is a synthetic corticosteroid. Budesonide is designated chemically as (RS)-11β, 16α, 17,21-tetrahydroxypregna-1,4-diene-3,20-dione cyclic 16,17-acetal with butyraldehyde. Budesonide is provided as a mixture of two epimers (22R and 22S). The molecular formula of budesonide is C H O and its molecular weight is 430.5. Its structural formula is:25346

Budesonide, USP is a white to almost white crystalline powder that is freely soluble in methylene chloride, sparingly soluble in alcohol and practically insoluble in water. Its partition coefficient between octanol and water at pH 5 is 1.6 x 10 ionic strength 0.01.^3

Each capsule for oral administration contains 3 mg of micronized budesonide with the following inactive ingredients: acetyltributyl citrate, colloidal silicon dioxide, crospovidone, dimethicone, ethylcellulose, FD&C Red No. 40 Aluminum Lake, gelatin, lactose monohydrate, magnesium stearate, methacrylic acid copolymer type C, polysorbate 80, sodium hydroxide, sodium lauryl sulfate, talc, titanium dioxide and triethyl citrate.

The imprinting ink contains the following: black iron oxide, D&C Yellow No. 10 Aluminum Lake, FD&C Blue No. 1 Aluminum Lake, FD&C Blue No. 2 Aluminum Lake, FD&C Red No. 40 Aluminum Lake, Propylene Glycol and shellac glaze.

12 CLINICAL PHARMACOLOGY

12.1 Mechanism of Action

Budesonide has a high topical glucocorticosteroid (GCS) activity and a substantial first pass elimination. The formulation contains granules which are coated to protect dissolution in gastric juice, but which dissolve at pH greater than 5.5, i.e., normally when the granules reach the duodenum. Thereafter, a matrix of ethylcellulose with budesonide controls the release of the drug into the intestinal lumen in a time-dependent manner.

12.2 Pharmacodynamics

Budesonide has a high glucocorticoid effect and a weak mineralocorticoid effect, and the affinity of budesonide to GCS receptors, which reflects the intrinsic potency of the drug, is about 200-fold that of cortisol and 15-fold that of prednisolone.

Treatment with systemically active GCS is associated with a suppression of endogenous cortisol concentrations and an impairment of the hypothalamus-pituitary-adrenal (HPA) axis function. Markers, indirect and direct, of this are cortisol levels in plasma or urine and response to ACTH stimulation.

Plasma cortisol suppression was compared following 5 days’ administration of budesonide capsules (enteric coated) and prednisolone in a crossover study in healthy volunteers. The mean decrease in the integrated 0 to 24 hour plasma cortisol concentration was greater (78%) with prednisolone 20 mg per day compared to 45% with budesonide capsules (enteric coated) 9 mg per day.

12.3 Pharmacokinetics

Absorption

The absorption of budesonide capsules (enteric coated) seems to be complete, although C and T are variable. Time to peak concentration varies in individual patients between 30 and 600 minutes. Following oral administration of 9 mg of budesonide in healthy subjects, a peak plasma concentration of approximately 5 nmol/L is observed and the area under the plasma concentration time curve is approximately 30 nmol•hr/L. The systemic availability after a single dose is higher in patients with Crohn's disease compared to healthy volunteers, (21% vs 9%) but approaches that in healthy volunteers after repeated dosing.maxmax

Distribution

The mean volume of distribution (V) of budesonide varies between 2.2 and 3.9 L/kg in healthy subjects and in patients. Plasma protein binding is estimated to be 85 to 90% in the concentration range 1 to 230 nmol/L, independent of gender. The erythrocyte/plasma partition ratio at clinically relevant concentrations is about 0.8.ss

Metabolism

Following absorption, budesonide is subject to high first pass metabolism (80% to 90%). experiments in human liver microsomes demonstrate that budesonide is rapidly and extensively biotransformed, mainly by CYP3A4, to its two major metabolites, 6β-hydroxy budesonide and 16α-hydroxy prednisolone. The glucocorticoid activity of these metabolites is negligible (less than 1/100) in relation to that of the parent compound. In vitro

investigations with intravenous doses in healthy subjects are in agreement with the findings and demonstrate that budesonide has a high plasma clearance, 0.9 to 1.8 L/min. Similarly, high plasma clearance values have been shown in patients with Crohn’s disease. These high plasma clearance values approach the estimated liver blood flow, and, accordingly, suggest that budesonide is a high hepatic clearance drug. In vivoin vitro

The plasma elimination half-life, t , after administration of intravenous doses ranges between 2 and 3.6 hours, and does not differ between healthy adults and patients with Crohn’s disease.1/2

Excretion

Budesonide is excreted in urine and feces in the form of metabolites. After oral as well as intravenous administration of micronized [ H]-budesonide, approximately 60% of the recovered radioactivity is found in urine. The major metabolites, including 6β-hydroxy budesonide and 16α-hydroxy prednisolone, are mainly renally excreted, intact or in conjugated forms. No unchanged budesonide is detected in urine.^3

Special Populations

Gender

No significant pharmacokinetic differences have been identified due to gender.

Hepatic Insufficiency

In patients with liver cirrhosis, systemic availability of orally administered budesonide correlates with disease severity and is, on average, 2.5-fold higher compared with healthy controls. Patients with mild liver disease are minimally affected. Patients with severe liver dysfunction were not studied. Absorption parameters are not altered, and for the intravenous dose, no significant differences in CL or V are observed.ss

Renal Insufficiency

The pharmacokinetics of budesonide in patients with renal impairment has not been studied. Intact budesonide is not renally excreted, but metabolites are to a large extent, and might therefore reach higher levels in patients with impaired renal function. However, these metabolites have negligible corticosteroid activity as compared with budesonide (less than 1/100).

Drug-Drug Interactions

Budesonide is metabolized via CYP3A4. Potent inhibitors of CYP3A4 can increase the plasma levels of budesonide several-fold. Co-administration of ketoconazole results in an 8-fold increase in AUC of budesonide, compared to budesonide alone. Grapefruit juice, an inhibitor of gut mucosal CYP3A, approximately doubles the systemic exposure of oral budesonide. Conversely, induction of CYP3A4 can result in the lowering of budesonide plasma levels.

Oral contraceptives containing ethinyl estradiol, which are also metabolized by CYP3A4, do not affect the pharmacokinetics of budesonide. Budesonide does not affect the plasma levels of oral contraceptives (i.e., ethinyl estradiol) [ ]. see Drug Interactions (7)

Since the dissolution of the coating of budesonide capsules (enteric coated) is pH dependent (dissolves at pH greater than 5.5), the release properties and uptake of the compound may be altered after treatment with drugs that change the gastrointestinal pH. However, the gastric acid inhibitory drug omeprazole, 20 mg once daily does not affect the absorption or pharmacokinetics of budesonide capsules (enteric coated). When an uncoated oral formulation of budesonide is co-administered with a daily dose of cimetidine 1 g, a slight increase in the budesonide peak plasma concentration and rate of absorption occurs, resulting in significant cortisol suppression.

Food Effects

A mean delay in time to peak concentration of 2.5 hours is observed with the intake of a high-fat meal, with no significant differences in AUC.

13 NONCLINICAL TOXICOLOGY

13.1 Carcinogenesis, Mutagenesis, Impairment of Fertility

Carcinogenicity studies with budesonide were conducted in rats and mice. In a 2-year study in Sprague-Dawley rats, budesonide caused a statistically significant increase in the incidence of gliomas in male rats at an oral dose of 50 mcg/kg (approximately 0.05 times the maximum recommended human dose on a body surface area basis). In addition, there were increased incidences of primary hepatocellular tumors in male rats at 25 mcg/kg (approximately 0.023 times the maximum recommended human dose on a body surface area basis) and above. No tumorigenicity was seen in female rats at oral doses up to 50 mcg/kg (approximately 0.05 times the maximum recommended human dose on a body surface area basis). In an additional 2-year study in male Sprague-Dawley rats, budesonide caused no gliomas at an oral dose of 50 mcg/kg (approximately 0.05 times the maximum recommended human dose on a body surface area basis). However, it caused a statistically significant increase in the incidence of hepatocellular tumors at an oral dose of 50 mcg/kg (approximately 0.05 times the maximum recommended human dose on a body surface area basis). The concurrent reference corticosteroids (prednisolone and triamcinolone acetonide) showed similar findings. In a 91-week study in mice, budesonide caused no treatment-related carcinogenicity at oral doses up to 200 mcg/kg (approximately 0.1 times the maximum recommended human dose on a body surface area basis).

Budesonide was not genotoxic in the Ames test, the mouse lymphoma cell forward gene mutation (TK) test, the human lymphocyte chromosome aberration test, the sex-linked recessive lethality test, the rat hepatocyte UDS test and the mouse micronucleus test.+/- Drosophila melanogaster

In rats, budesonide had no effect on fertility at subcutaneous doses up to 80 mcg/kg (approximately 0.07 times the maximum recommended human dose on a body surface area basis). However, it caused a decrease in prenatal viability and viability in pups at birth and during lactation, along with a decrease in maternal body-weight gain, at subcutaneous doses of 20 mcg/kg (approximately 0.02 times the maximum recommended human dose on a body surface area basis) and above. No such effects were noted at 5 mcg/kg (approximately 0.005 times the maximum recommended human dose on a body surface area basis).

14 CLINICAL STUDIES

The safety and efficacy of budesonide capsules (enteric coated)were evaluated in 994 patients with mild to moderate active Crohn’s disease of the ileum and/or ascending colon in five randomized and double-blind studies. The study patients ranged in age from 17 to 85 (mean 35), 40% were male and 97% were white. Of the 651 patients treated with budesonide capsules (enteric coated), 17 (2.6%) were greater than or equal to 65 years of age and none were greater than 74 years of age. The Crohn’s Disease Activity Index (CDAI) was the main clinical assessment used for determining efficacy in these five studies. The CDAI is a validated index based on subjective aspects rated by the patient (frequency of liquid or very soft stools, abdominal pain rating and general well-being) and objective observations (number of extraintestinal symptoms, need for antidiarrheal drugs, presence of abdominal mass, body weight and hematocrit). Clinical improvement, defined as a CDAI score of less than or equal to 150 assessed after 8 weeks of treatment, was the primary efficacy variable in these five comparative efficacy studies of budesonide capsules (enteric coated). Safety assessments in these studies included monitoring of adverse reactions. A checklist of potential symptoms of hypercorticism was used.

One study (Study 1) compared the safety and efficacy of budesonide capsules (enteric coated) 9 mg daily in the morning to a comparator. At baseline, the median CDAI was 272. Budesonide capsules (enteric coated) 9 mg daily resulted in a significantly higher clinical improvement rate at Week 8 than the comparator. See Table 4.

Table 4. Clinical Improvement Rates (CDAI less than or equal to 150) After 8 Weeks of Treatment
Clinical | Budesonide Capsules (Enteric Coated) |  | Comparator [This drug is not approved for the treatment of Crohn’s disease in the United States.] | Placebo | Prednisolone
Study | 9 mg Daily | 4.5 mg Twice Daily | Comparator [This drug is not approved for the treatment of Crohn’s disease in the United States.] | Placebo | Prednisolone
1 | 62/91 (69%) |  | 37/83 (45%)
2 |  | 31/61 (51%) |  | 13/64 (20%)
3 | 38/79 (48%) | 41/78 (53%) |  | 13/40 (33%)
4 | 35/58 (60%) | 25/60 (42%) |  |  | 35/58 (60%)
5 | 45/86 (52%) |  |  |  | 56/85 (65%)

Two placebo-controlled clinical trials (Studies 2 and 3) were conducted. Study 2 involved 258 patients and tested the effects of graded doses of budesonide capsules (enteric coated) (1.5 mg twice daily, 4.5 mg twice daily, or 7.5 mg twice daily) versus placebo. At baseline, the median CDAI was 290. The 3 mg per day dose level (data not shown) could not be differentiated from placebo. The 9 mg per day arm was statistically different from placebo (Table 4), while no additional benefit was seen when the daily budesonide capsule (enteric coated) dose was increased to 15 mg per day (data not shown). In Study 3, the median CDAI at baseline was 263. Neither 9 mg daily nor 4.5 mg twice daily budesonide capsule (enteric coated) dose levels was statistically different from placebo (Table 4).

Two clinical trials (Studies 4 and 5) compared budesonide capsules (enteric coated) with oral prednisolone (initial dose 40 mg per day). At baseline, the median CDAI was 277. Equal clinical improvement rates (60%) were seen in the budesonide capsules (enteric coated) 9 mg daily and the prednisolone groups in Study 4. In Study 5, 13% fewer patients in the budesonide capsules (enteric coated) group experienced clinical improvement than in the prednisolone group (no statistical difference) (Table 4).

The proportion of patients with normal plasma cortisol values (greater than 150 nmol/L) was significantly higher in the budesonide capsule (enteric coated) groups in both trials (60% to 66%) than in the prednisolone groups (26% to 28%) at Week 8.

The efficacy and safety of budesonide capsules (enteric coated) for maintenance of clinical remission were evaluated in four double-blind, placebo-controlled, 12-month trials in which 380 patients were randomized and treated once daily with 3 mg or 6 mg budesonide capsules (enteric coated) or placebo. Patients ranged in age from 18 to 73 (mean 37) years. Sixty percent of the patients were female and 99% were Caucasian. The mean CDAI at entry was 96. Among the four clinical trials, approximately 75% of the patients enrolled had exclusively ileal disease. Colonoscopy was not performed following treatment. Budesonide capsules (enteric coated) 6 mg per day prolonged the time to relapse, defined as an increase in CDAI of at least 60 units to a total score greater than 150 or withdrawal due to disease deterioration. The median time to relapse in the pooled population of the four studies was 154 days for patients taking placebo, and 268 days for patients taking budesonide capsules (enteric coated) 6 mg per day. Budesonide capsules (enteric coated) 6 mg per day reduced the proportion of patients with loss of symptom control relative to placebo in the pooled population for the four studies at 3 months (28% vs. 45% for placebo).

16 HOW SUPPLIED/STORAGE AND HANDLING

NDC:68151-4374-0 in a PACKAGE of 1 CAPSULES

17 PATIENT COUNSELING INFORMATION

“See FDA-Approved Patient Labeling ()” Patient Information

Patients being treated with budesonide capsules (enteric coated) should receive the following information and instructions. This information is intended to aid the patient in the safe and effective use of the medication. It is not a disclosure of all possible adverse or intended effects. For proper use of budesonide capsules (enteric coated) and to attain maximum improvement, the patient should read and follow the accompanying FDA-Approved Patient Labeling.

17.1 Hypercorticism and Adrenal Suppression

Patients should be advised that budesonide capsules (enteric coated) may cause systemic glucocorticosteroid effects of hypercorticism and adrenal suppression. Patients should taper slowly from systemic glucocorticosteroids if transferring to budesonide capsules (enteric coated) [ ]. see and Warnings and Precautions (5.1) (5.2)

17.2 Immunosuppression

Patients who are on immunosuppressant doses of glucocorticosteroids should be warned to avoid exposure to chicken pox or measles and, if exposed, to consult their physician without delay. Patients should be informed of potential worsening of existing tuberculosis, fungal, bacterial, viral or parasitic infections [ ]. see Warnings and Precautions (5.3)

17.3 How to Take Budesonide Capsules (enteric coated)

Budesonide capsules (enteric coated) should be swallowed whole and NOT CHEWED OR BROKEN. Patients should be advised to avoid the consumption of grapefruit juice for the duration of their budesonide capsules (enteric coated) therapy.

PATIENT INFORMATION

PATIENT INFORMATION LEAFLET BUDESONIDE CAPSULES (enteric coated) (bue des' oh nide) 3 mg

Read the Patient Information that comes with budesonide capsules (enteric coated) before you start taking it and each time you get a refill. There may be new information. This information does not take the place of talking with your healthcare provider about your medical condition or your treatment.

What are budesonide capsules (enteric coated)?

Budesonide capsules (enteric coated) are a prescription glucocorticosteroid medicine used in people with mild to moderate Crohn’s disease that affects part of the small intestine (ileum) and part of the large intestine (ascending colon):

- to treat active Crohn’s disease
- to help keep symptoms from coming back for up to 3 months.

It is not known if budesonide capsules (enteric coated) are safe and effective in children.

Who should not take budesonide capsules (enteric coated)?

Do not take budesonide capsules (enteric coated) if:

- you are allergic to budesonide or any of the ingredients in budesonide capsules (enteric coated). See the end of this leaflet for a complete list of ingredients in budesonide capsules (enteric coated).

What should I tell my healthcare provider before taking budesonide capsules (enteric coated)?

: Before you take budesonide capsules (enteric coated) tell your healthcare provider if you

- have liver problems
- are planning to have surgery
- have chicken pox or measles or have recently been near anyone with chicken pox or measles
- have or had a family history of diabetes, cataracts or glaucoma
- have or had tuberculosis
- have high blood pressure (hypertension)
- have decreased bone mineral density (osteoporosis)
- stomach ulcers
- any other medical condition
- are pregnant or plan to become pregnant. It is not known if budesonide capsules (enteric coated) may harm your unborn baby.
- are breastfeeding or plan to breastfeed. Budesonide can pass into breast milk and may harm your baby. You and your healthcare provider should decide if you will take budesonide capsules (enteric coated) or breastfeed. You should not do both.

including prescription and non-prescription medicines, vitamins, and herbal supplements. Budesonide capsules (enteric coated) and other medicines may affect each other causing side effects. Tell your healthcare provider about all the medicines you take,

Especially tell your healthcare provider if you take:

- a glucocorticosteroid medicine
- medicines that suppress your immune system (immunosuppressant)
- ketoconazale or other medicines that affect how your liver works.

Ask your healthcare provider or pharmacist if you are not sure if your medicine is one listed above.

How should I take budesonide capsules (enteric coated)?

- Take budesonide capsules (enteric coated) exactly as your healthcare provider tells you.
- Your healthcare provider will tell you how many budesonide capsules (enteric coated) to take. Your healthcare provider may change your dose if needed.
- Take budesonide capsules (enteric coated) in the morning.
- Take budesonide capsules (enteric coated) whole. Do not chew or crush budesonide capsules (enteric coated) before swallowing.

What should I avoid while taking budesonide capsules (enteric coated)?

- Do not eat grapefruit or drink grapefruit juice while taking budesonide capsules (enteric coated). Eating grapefruit or drinking grapefruit juice can increase the level of budesonide in your blood.

What are the possible side effects of budesonide capsules (enteric coated)?

- Long-time use of budesonide capsules (enteric coated) can cause you to have too much glucocorticosteroid medicine in your blood. Tell your healthcare provider if you have any of the following signs and symptoms of hypercorticism: Effects of having too much glucocorticosteroid medicine in your blood (hypercorticism).
  - acne
  - bruise easily
  - rounding of your face (moon face)
  - ankle swelling
  - thicker or more hair on your body and face
  - a fatty pad or hump between your shoulders (buffalo hump)
  - pink or purple stretch marks on the skin of your abdomen, thighs, breasts and arms
- When budesonide capsules (enteric coated) are taken for a long period of time (chronic use), adrenal suppression can happen. This is a condition in which the adrenal glands do not make enough steroid hormones. Symptoms of adrenal suppression include: tiredness, weakness, nausea and vomiting and low blood pressure. Tell your healthcare provider if you are under stress or have any symptoms of adrenal suppression during treatment with budesonide capsules (enteric coated). Adrenal suppression.
- Budesonide capsules (enteric coated) weaken your immune system. Taking medicines that weaken your immune system makes you more likely to get infections. Avoid contact with people who have contagious diseases such as chicken pox or measles, while taking budesonide capsules (enteric coated). Tell your healthcare provider about any signs or symptoms of infection during treatment with budesonide capsules (enteric coated), including: Immune system effects and a higher chance of infections.
  - fever
  - pain
  - aches
  - chills
  - feeling tired
  - nausea and vomiting
- If you take certain other glucocorticosteroid medicines to treat allergies, switching to budesonide capsules (enteric coated) may cause your allergies to come back. These allergies may include eczema (a skin disease) or rhinitis (inflammation inside your nose). Tell your healthcare provider if any of your allergies become worse while taking budesonide capsules (enteric coated). Worsening of allergies.

The most common side effects of budesonide capsules (enteric coated) include:

- headache
- infection in your air passages (respiratory infection)
- back pain
- upset stomach
- dizziness
- abdominal pain
- excessive stomach or intestinal gas
- diarrhea
- sinus infection
- viral infection
- joint pain

Tell your healthcare provider if you have any side effect that bothers you or that does not go away.

These are not all the possible side effects of budesonide capsules (enteric coated). For more information, ask your healthcare provider or pharmacist.

Call your healthcare provider for medical advice about side effects. You may report side effects to Mylan Pharmaceuticals Inc. at 1-877-446-3679 (1-877-4-INFO-RX) or FDA at 1-800-FDA-1088 or www.fda.gov/medwatch.

How should I store budesonide capsules (enteric coated)?

- Store budesonide capsules (enteric coated) at 20° to 25°C (68° to 77°F).
- Keep budesonide capsules (enteric coated) in a tightly closed container.

Keep budesonide capsules (enteric coated) and all medicines out of reach from children.

General information about budesonide capsules (enteric coated).

Medicines are sometimes prescribed for purposes other than those listed in Patient Information leaflets. Do not use budesonide capsules (enteric coated) for a condition for which it was not prescribed. Do not give budesonide capsules (enteric coated) to other people, even if they have the same symptoms you have. It may harm them.

This Patient Information leaflet summarizes the most important information about budesonide capsules (enteric coated). If you would like more information, talk with your healthcare provider. You can ask your healthcare provider or pharmacist for information about budesonide capsules (enteric coated) that is written for health professionals.

For more information call Mylan Pharmaceuticals Inc. at 1-877-446-3679 (1-877-4-INFO-RX).

What are the ingredients in budesonide capsules (enteric coated)?

Active ingredient: budesonide, USP

Inactive ingredients: acetyltributyl citrate, colloidal silicon dioxide, crospovidone, dimethicone, ethylcellulose, FD&C Red No. 40 Aluminum Lake, gelatin, lactose monohydrate, magnesium stearate, methacrylic acid copolymer type C, polysorbate 80, sodium hydroxide, sodium lauryl sulfate, talc, titanium dioxide and triethyl citrate.

The imprinting ink contains the following: black iron oxide, D&C Yellow No. 10 Aluminum Lake, FD&C Blue No. 1 Aluminum Lake, FD&C Blue No. 2 Aluminum Lake, FD&C Red No. 40 Aluminum Lake, Propylene Glycol and shellac glaze.

This Patient Information has been approved by the U.S. Food and Drug Administration.

Morgantown, WV 26505 U.S.A. Mylan Pharmaceuticals Inc.

REVISED FEBRUARY 2014 BUDE:R2ppt